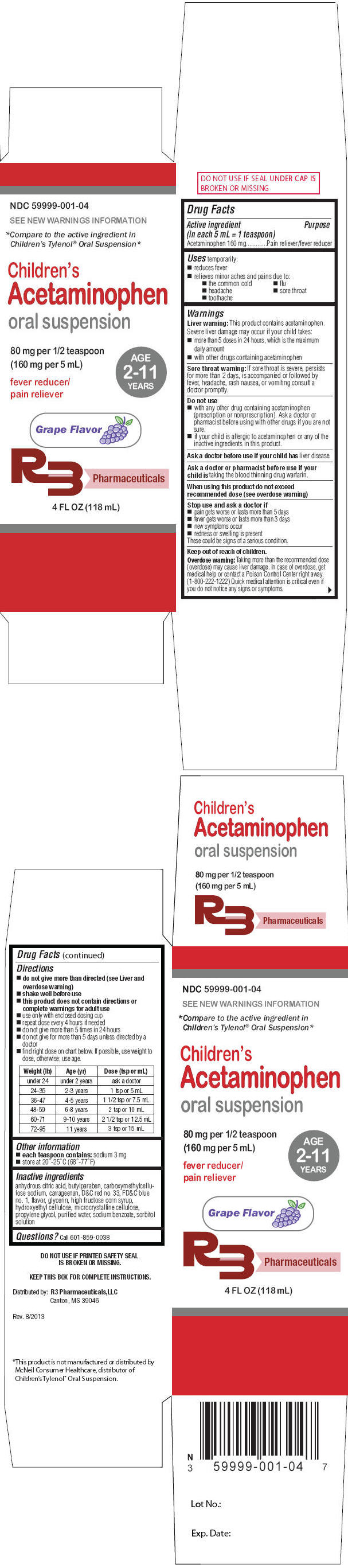 DRUG LABEL: Childrens Acetaminophen
NDC: 59999-001 | Form: SUSPENSION
Manufacturer: R3 Pharmaceuticals, LLC
Category: otc | Type: HUMAN OTC DRUG LABEL
Date: 20130925

ACTIVE INGREDIENTS: Acetaminophen 160 mg/5 mL
INACTIVE INGREDIENTS: ANHYDROUS CITRIC ACID; BUTYLPARABEN; CARBOXYMETHYLCELLULOSE SODIUM; CARRAGEENAN; D&C RED NO. 33; FD&C BLUE NO. 1; GLYCERIN; HIGH FRUCTOSE CORN SYRUP; HYDROXYETHYL CELLULOSE (100 MPA.S AT 2%); CELLULOSE, MICROCRYSTALLINE; PROPYLENE GLYCOL; WATER; SODIUM BENZOATE; SORBITOL

Children's Acetaminophen Oral Suspension

Drug Facts

Active ingredient (in each 5 mL = 1 teaspoon)

Acetaminophen 160 mg

Purpose

Pain reliever/fever reducer

Uses

temporarily:

- reduces fever
- relieves minor aches and pains due to:
  - the common cold
  - flu
  - headache
  - sore throat
  - toothache

Warnings

Liver warning

This product contains acetaminophen. Severe liver damage may occur if your child takes:

- more than 5 doses in 24 hours, which is the maximum daily amount
- with other drugs containing acetaminophen

Sore throat warning

If sore throat is severe, persists for more than 2 days, is accompanied or followed by fever, headache, rash nausea, or vomiting consult a doctor promptly.

Do not use

- with any other drug containing acetaminophen (prescription or nonprescription). Ask a doctor or pharmacist before using with other drugs if you are not sure.
- if your child is allergic to acetaminophen or any of the inactive ingredients in this product.

Ask a doctor before use if your child has liver disease.

Ask a doctor or pharmacist before use if your child is taking the blood thinning drug warfarin.

When using this product do not exceed recommended dose (see overdose warning)

Stop use and ask a doctor if

- pain gets worse or lasts more than 5 days
- fever gets worse or lasts more than 3 days
- new symptoms occur
- redness or swelling is present

These could be signs of a serious condition.

Keep out of reach of children.

Overdose warning

Taking more than the recommended dose (overdose) may cause liver damage. In case of overdose, get medical help or contact a Poison Control Center right away. (1-800-222-1222) Quick medical attention is critical even if you do not notice any signs or symptoms.

Directions

- do not give more than directed (see Liver and overdose warning)
- shake well before use
- this product does not contain directions or complete warnings for adult use
- use only with enclosed dosing cup
- repeat dose every 4 hours if needed
- do not give more than 5 times in 24 hours
- do not give for more than 5 days unless directed by a doctor
- find right dose on chart below. If possible, use weight to dose, otherwise; use age.

Weight (lb) | Age (yr) | Dose (tsp or mL)
under 24 | under 2 years | ask a doctor
24-35 | 2-3 years | 1 tsp or 5 mL
36-47 | 4-5 years | 1 1/2 tsp or 7.5 mL
48-59 | 6-8 years | 2 tsp or 10 mL
60-71 | 9-10 years | 2 1/2 tsp or 12.5 mL
72-95 | 11 years | 3 tsp or 15 mL

Other information

- each teaspoon contains: sodium 3 mg
- store at 20°-25°C (68°-77°F)

Inactive ingredients

anhydrous citric acid, butylparaben, carboxymethylcellulose sodium, carrageenan, D&C red no. 33, FD&C blue no. 1, flavor, glycerin, high fructose corn syrup, hydroxyethyl cellulose, microcrystalline cellulose, propylene glycol, purified water, sodium benzoate, sorbitol solution

Questions?

Call 601-859-0038

Distributed by: R3 Pharmaceuticals,LLC
Canton, MS 39046

PRINCIPAL DISPLAY PANEL - 118 mL Bottle Carton

NDC 59999-001-04

SEE NEW WARNINGS INFORMATION

*Compare to the active ingredient in
Children's Tylenol® Oral Suspension*

Children's
Acetaminophen
oral suspension

80 mg per 1/2 teaspoon
(160 mg per 5 mL)

fever reducer/
pain reliever

AGE
2-11
YEARS

Grape Flavor

R3 Pharmaceuticals

4 FL OZ (118 mL)